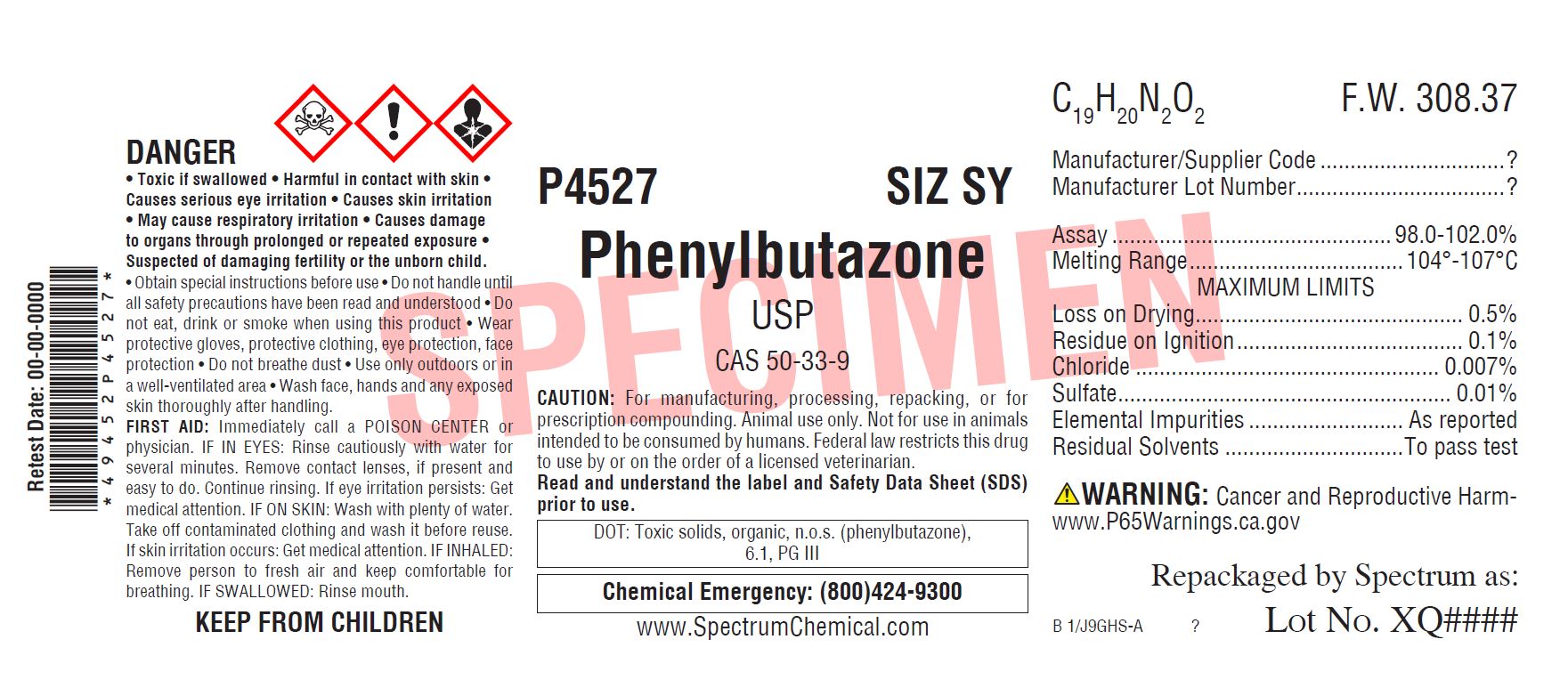 DRUG LABEL: Phenylbutazone
NDC: 49452-5286 | Form: POWDER
Manufacturer: Spectrum Laboratory Products, Inc.
Category: other | Type: BULK INGREDIENT
Date: 20211129

ACTIVE INGREDIENTS: PHENYLBUTAZONE 1 g/1 g

Phenylbutazone, For Vet Use